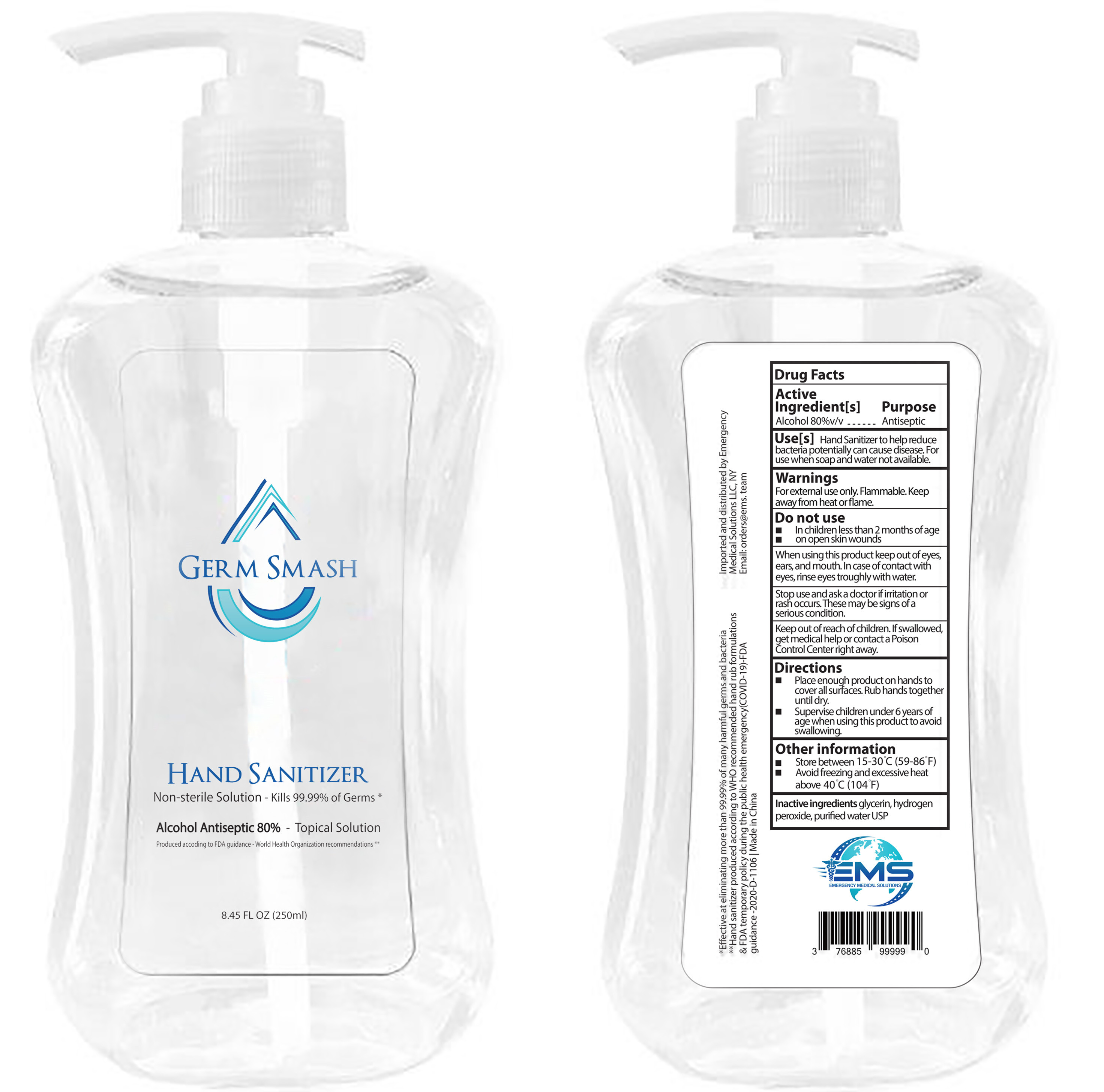 DRUG LABEL: Hand Sanitizer
NDC: 55467-006 | Form: LIQUID
Manufacturer: INTENTLY (GUANGZHOU) BIOTECHNOLOGY CO., LTD.
Category: otc | Type: HUMAN OTC DRUG LABEL
Date: 20200614

ACTIVE INGREDIENTS: ALCOHOL 200 mL/250 mL
INACTIVE INGREDIENTS: WATER; HYDROGEN PEROXIDE; GLYCERIN; TERT-BUTYL ALCOHOL; DENATONIUM BENZOATE

DOSAGE AND ADMINISTRATION

Store between 15-30°C(59-86°F)

Avoid feezing and excessive heat above40°C (104°F)

INACTIVE INGREDIENT

Water

Glycerin

Hydrogen Peroxide

Tert-butyl alcohol

Denatonium benzoate

INDICATIONS AND USAGE

Place enough product on hands to cover all surfaces.Rub hands together until dry.

ACTIVE INGREDIENT

Ethanol

keep out of reach of children

PURPOSE

Disinfection
Sterilization
No Rinseing

WARNINGS

For external use only.Flammable. Keep away from heat or flame.